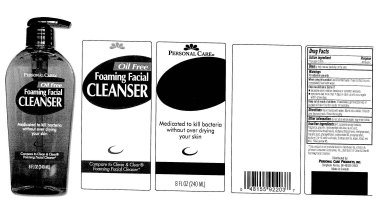 DRUG LABEL: Personal Care Oil Free Foaming Facial Cleanser
                        
NDC: 29500-7010 | Form: LIQUID
Manufacturer: Personal Care Products, Inc
Category: otc | Type: HUMAN OTC DRUG LABEL
Date: 20120109

ACTIVE INGREDIENTS: TRICLOSAN 0.25 mL/100 mL
INACTIVE INGREDIENTS: COCAMIDOPROPYL BETAINE; GLYCERIN; HYDROXYETHYL CELLULOSE (140 CPS AT 5%); LAURIC ACID; METHYLISOTHIAZOLINONE; METHYLPARABEN; MYRISTIC ACID; PHENOXYETHANOL; POLYSORBATE 20; PROPYLPARABEN; TROLAMINE; WATER; FD&C RED NO. 40; FD&C YELLOW NO. 5

Personal Care Oil Free Foaming Facial Cleanser

Active Ingredient Purpose

Triclosan 0.25 percent Antiseptic

Uses

to help reduce bacteria on the skin

Warnings

For external use only.

INDICATIONS AND USAGE

Uses to help reduce bacteria on the skin

Stop use and ask a doctor if

excessive skin irritation develops or condition worsens

symptoms last more than 7 days or clear up and occur again within a few days

Keep out of reach of children

If swallowed, get medical help or contact a Poison Control Center immediately.

Directions

Mix in hands with water. Work into a lather.

Smooth over face and neck. Rinse thoroughly

Other information

do not store where water may enter bottle

Inactive Ingredients

B-IT, cocamiccpropyl betaine, fragrance, glycerin, hydroxyethyl cellulose, lauric acid,

methy chloroisothiazolinone, methylisothizolinone, methylparaben, myristic acid, phenoxyethanol,

polysorbate-20, propylparaben, sodium C14-16 olefin sulfonate, triethanolamine, water, FD and C red 40, FD and C yellow 5

DESCRIPTION

This product is not manufactured or distributed by Johnson and Johnson Consumer Companies Inc.,

distributor of Clean and Clear Foaming Facial Cleanser

Distributed by:

Personal Care Products, Inc.

Bingham Farms, MI 48025-2463

Made in Canada

PACKAGE LABEL

Personal Care

Oil Free

Foaming Facial

CLEANSER

Medicated to kill bacteria

without over drying your skin

Compare to Clean and Clear

Foaming Facial Cleaner

8 FL OZ (240 ML)